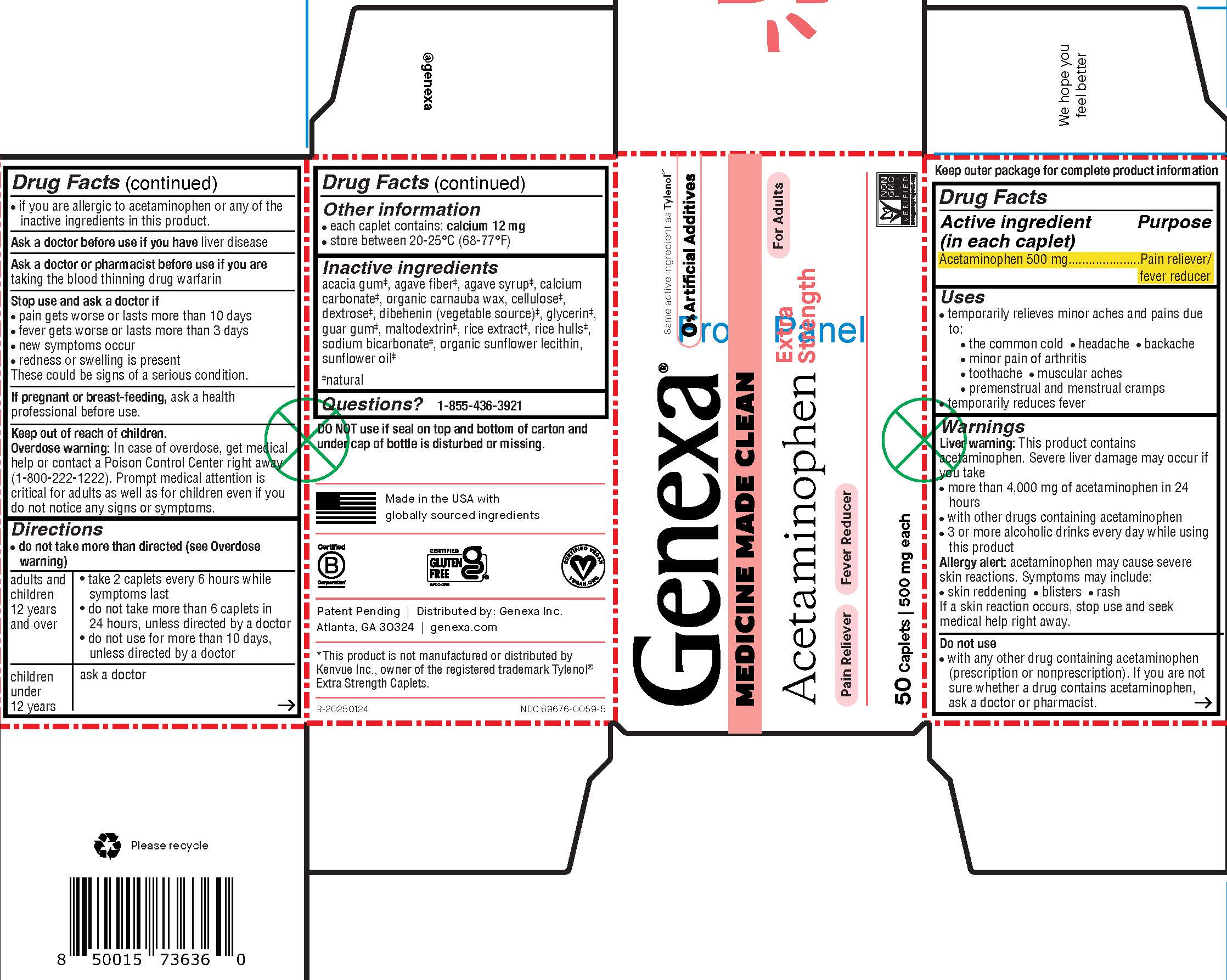 DRUG LABEL: Genexa Acetaminophen
NDC: 69676-0059 | Form: TABLET, COATED
Manufacturer: Genexa Inc.
Category: otc | Type: HUMAN OTC DRUG LABEL
Date: 20250605

ACTIVE INGREDIENTS: ACETAMINOPHEN 500 mg/1 1
INACTIVE INGREDIENTS: INULIN; ACACIA; GUAR GUM; AGAVE TEQUILANA JUICE; CARNAUBA WAX; DEXTROSE; MALTODEXTRIN; SODIUM BICARBONATE; LECITHIN, SUNFLOWER; CALCIUM CARBONATE; RICE BRAN; GLYCERYL DIBEHENATE; SUNFLOWER OIL; POWDERED CELLULOSE; GLYCERIN

Acetaminophen Extra Strength Caplets

Drug Facts

Active ingredient (in each caplet)

Acetaminophen 500 mg

Purpose

Pain reliever/fever reducer

Uses

- temporarily relieves minor aches and pains due to:
  - the common cold
  - headache
  - backache
  - minor pain of arthritis
  - toothache
  - muscular aches
  - premenstrual and menstrual cramps
- temporarily reduces fever

Warnings

Liver warning: This product contains acetaminophen.

Severe liver damage may occur if you take

- more than 4,000 mg of acetaminophen in 24 hours
- with other drugs containing acetaminophen
- 3 or more alcoholic drinks every day while using this product

Allergy alert: acetaminophen may cause severe skin reactions. Symptoms may include:

- skin reddening
- blisters
- rash

If a skin reaction occurs, stop use and seek medical help right away.

Do not use

- with any other drug containing acetaminophen (prescription or nonprescription). If you are not sure whether a drug contains acetaminophen, ask a doctor or pharmacist
- if you are allergic to acetaminophen or any of the inactive ingredients in this product.

Ask a doctor before use if you have liver disease

Ask a doctor or pharmacist before use if you are taking the blood thinning drug warfarin

Stop use and ask a doctor if

- pain gets worse or lasts more than 10 days
- fever gets worse or lasts more than 3 days
- new symptoms occur
- redness or swelling is present

These could be signs of a serious condition.

PREGNANCY OR BREAST FEEDING

If pregnant or breast-feeding, ask a health professional before use.

Keep out of reach of children.

OVERDOSAGE

Overdose warning: In case of overdose, get medical help or contact a Poison Control Center right away (1-800-222-1222). Prompt medical attention is critical for adults as well as for children even if you do not notice any signs or symptoms.

Directions

• do not take more than directed (see Overdose warning)

adults and children 12 years and over

- take 2 caplets every 6 hours while symptoms last
- do not take more than 6 caplets in 24 hours, unless directed by a doctor
- do not use for more than 10 days, unless directed by a doctor

children under 12 years

ask a doctor

Other information

- each caplet contains: calcium 12 mg
- store between 20-25°C (68-77°F)

Inactive ingredients

acacia gum‡, agave fiber‡, agave syrup‡, calcium carbonate‡, organic carnauba wax, cellulose‡, dextrose‡, dibehenin (vegetable source)‡, glycerin‡, guar gum‡, maltodextrin‡, rice extract‡, rice hulls‡, sodium bicarbonate‡, organic sunflower lecithin, sunflower oil‡

‡natural

Questions? 1-855-436-3921

DO NOT use if seal on top and bottom of carton or under cap of bottle is disturbed or missing.

Made in the USA with globally sourced ingredients

Patent Pending | Distributed by: Genexa Inc.

Atlanta, GA 30324 | genexa.com

*This product is not manufactured or distributed by Kenvue Inc., owner of the registered trademark Tylenol® Extra Strength Caplets.

NDC 69676-0059-5

PACKAGE LABEL

Genexa®

Same active ingredient as Tylenol®*

0% Artificial Additives

MEDICINE MADE CLEAN

For Adults

Acetaminophen Extra Strength

Pain Reliever

Fever Reducer

50 Caplets | 500 mg each